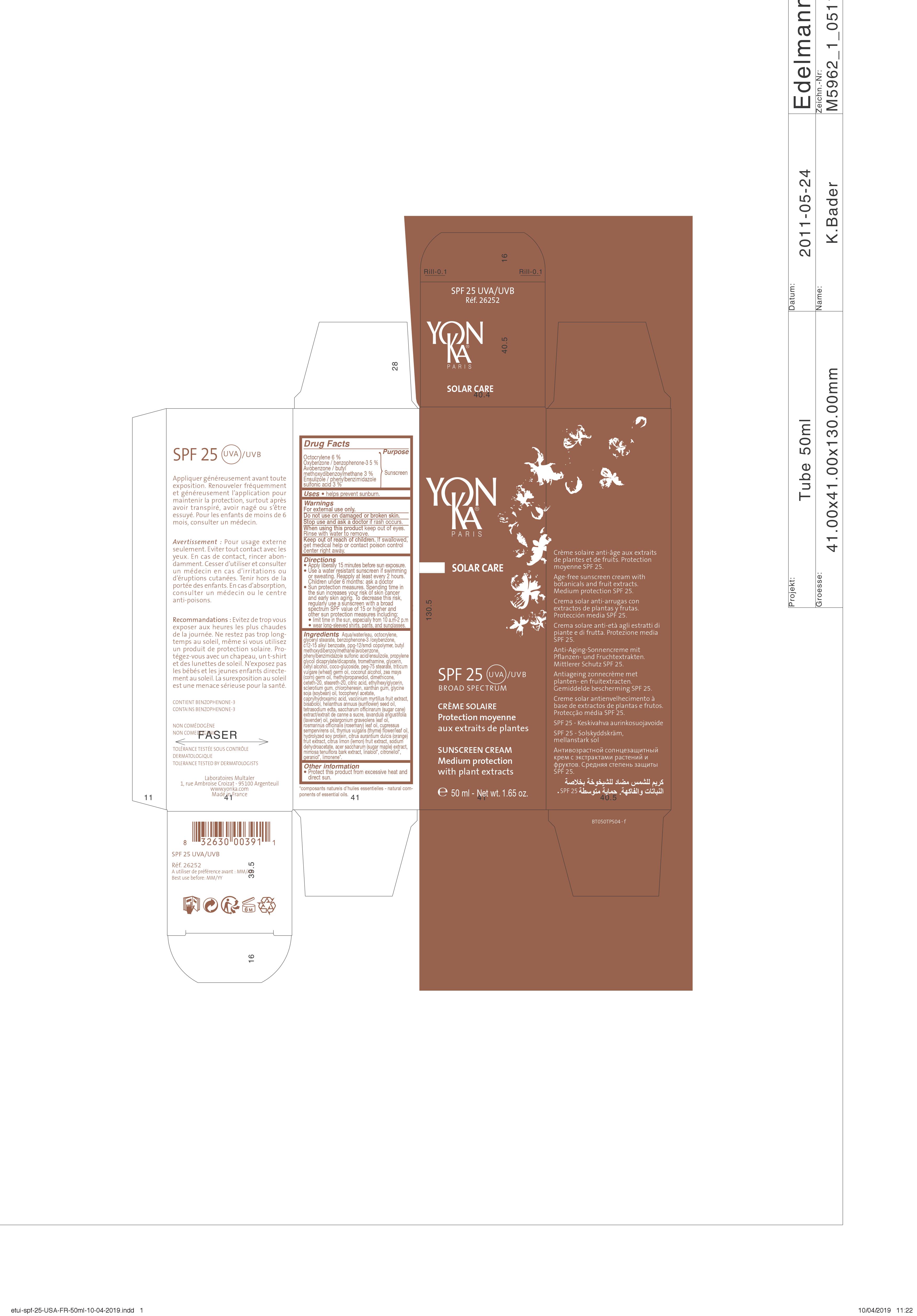 DRUG LABEL: SPF 25 UVA/UVB
NDC: 51191-3016 | Form: CREAM
Manufacturer: MULTALER ET CIE S.A.S.
Category: otc | Type: HUMAN OTC DRUG LABEL
Date: 20191212

ACTIVE INGREDIENTS: OCTOCRYLENE 6 g/100 g; OXYBENZONE 5 g/100 g; AVOBENZONE 3 g/100 g; ENSULIZOLE 3 g/100 g
INACTIVE INGREDIENTS: WATER; ALKYL (C12-15) BENZOATE; GLYCERIN; PEG-8/SMDI COPOLYMER; GLYCERYL MONOSTEARATE; PEG-75 STEARATE; PROPYLENE GLYCOL DICAPRYLATE/DICAPRATE; TROMETHAMINE; CETYL ALCOHOL; COCO GLUCOSIDE; .ALPHA.-BISABOLOL, (+/-)-; CHLORPHENESIN; XANTHAN GUM; EDETATE SODIUM; COCONUT ALCOHOL; CITRIC ACID MONOHYDRATE; .ALPHA.-TOCOPHEROL ACETATE; WHEAT GERM OIL; CORN OIL; DIMETHICONE; CETETH-20; STEARETH-20; SUGARCANE; ACER SACCHARUM SAP; BILBERRY; SUNFLOWER OIL; SOY PROTEIN; SOYBEAN OIL; MIMOSA TENUIFLORA BARK; ALMOND; LEMON; LAVENDER OIL; ROSMARINUS OFFICINALIS FLOWERING TOP OIL; CUPRESSUS SEMPERVIRENS LEAF OIL; THYME OIL; ORANGE; SODIUM DEHYDROACETATE; SODIUM BENZOATE; BETASIZOFIRAN; METHYLPROPANEDIOL; ETHYLHEXYLGLYCERIN; CAPRYLHYDROXAMIC ACID; PELARGONIUM GRAVEOLENS FLOWER OIL

DRUG FACTS

Active ingredients Purpose

Ensulizole 3% {

Oxybenzone 5% { Sunscreen

Avobenzone 3% {

Octocrylene 6% {

DESCRIPTION

SOLAR CARE

SPF 25 UVA/UVB

BROAD SPECTRUM

CREME SOLAIRE

Protection moyenne

aux extraits de plantes

SUNSCREEN CREAM

Medium protection

with plant extracts

Crème solaire anti-âge aux extraits

de plantes et de fruits. Protection

moyenne SPF 25.

Age free sunscreen cream with

botanicals and fruit extracts.

Medium protection SPF 25.

Crema solar anti-arrugas con

extractos de plantas y frutas.

Proteccion media SPF 25.

Anti-aging Sonnencreme mit

Pflanzen- und Fruchtextrakten.

Mittlerer Schutz SPF 25.

Crema solare anti-età agli estratti di

piante e di frutta. Protezione media

SPF 25.

Antiageing Zonnencrème met

planten- en fruitextracten.

Gemiddelde Bescherming SPF 25.

Creme solar antienvelhecimento à

base de extractos de plantas e frutos.

Protecçao média SPF 25.

Appliquer généreusement avant toute

exposition. Renouveler fréquemment

et généreusement l'application pour

maintenir la protection, surtout après

avoir transpiré, avoir nagé ou s'être

essuyé. Pour les enfants de moins de

6 mois, consulter un médecin.

Avertissement : Pour usage externe

seulement. Eviter tout contact avec les

yeux. En cas de contact, rincer abon-

damment. Cesser d'utiliser et consulter

un médecin en cas d'irritations ou

d'éruptions cutanées. Tenir hors de la

portée des enfants. En cas d'absorption,

consulter un médecin ou le centre

anti-poisons.

Recommandations : Eviter de trop vous

exposer aux heures les plus chaudes

de la journée. Ne restez pas trop long-

temps au soleil. même si vous utilisez

un produit de protection solaire. Pro-

tégez-vous avec un chapeau, un t-shirt

et des lunettes de soleil. N'exposez pas

les bébés et les jeunes enfants directe-

ment au soleil. La surexposition au soleil

est une menace sérieuse

pour la santé.

CONTIENT BENZOPHENONE-3

CONTAINS BENZOPHENONE-3

NON COMEDOGENE

NON COMEDOGENIC

TOLERANCE TESTEE SOUS CONTROLE DERMATOLOGIQUE

TOLERANCE TESTED BY DERMATOLOGISTS

WARNINGS AND PRECAUTIONS

Uses • hels prevent sunburn.

Warnings

For external use only.

Do not use on damaged or broken skin.

Stop use and ask a doctor if rash occurs.

When using this product keep out of eyes.

Rinse with water to remove.

Keep out of reach of children. If swallowed,

get medical help or contact poison control

center right away.

Directions

• Apply liberally 15 minutes before sun exposure.

• Use a water resistant sunscreen if swimming or

sweating. Reapply at least every 2 hours.

Children under 6 months : ask a doctor.

• Sun protection measures. Spending time in

the sun increases your risk of skin cancer

and early skin aging. To decrease this risk,

regularly use a sunscreen with a broad

sprectrum SPF value of 15 or higher and

other sun protection measures including:

• limit time in the sun, especially from 10 a.m-2p.m

• wear long-sleeved shirts, pants, and sunglasses.

Other information

• Protect this product from excessive heat and

direct sun.

Inactive ingredients Aqua/water/eau,

alkyl (C12-15) benzoate, glyceryl stearate, ppg-12/smdi

copolymer, propylene glycol dicaprylate/dicaprate,

tromethamine, glycerin, cetyl alcohol, coco-glucoside,

peg-75 stearate, triticum vulgare (wheat) germ oil,

coconut alcohol, zea mays (corn) oil, dimethicone,

ceteth-20, steareth-20, citric acid, sclerotium gum,

xanthan gum, helianthus annuus (sunflower) seed oil,

tocopheryl acetate, vaccinium myrtillus (bilberry) fruit

extract, bisabolol, glycine soja (soybean) oil,

hydrolyzed sweet almond protein, saccharum

officinarum (sugar cane) extract/extrait de canne a

sucre, lavandula angustifolia (lavender) oil, pelargonium

graveolens (geranium) leaf oil, rosmarinus officinalis

(rosemary) leaf oil, cupressus sempervirens (cypress) oil,

thymus vulgaris (thyme) flower/leaf oil, citrus limon fruit

extract / citrus medica limonum (lemon) fruit extract,

citrus aurantium dulcis (orange) fruit extract, hydrolyzed

soy protein, acer saccharum (sugar maple) extract,

mimosa tenuiflora bark extract, sodium hydroxide,

methylpropanediol, ethylhexylglycerin, chlorphenesin,

caprylhydroxamic acid, tetrasodium edta, sodium

dehydroacetate, sodium benzoate, linalool*, citronellol*,

geraniol*, limonene*.

*composants naturels d'huiles essentielles - natural com-

ponents of essentials oils